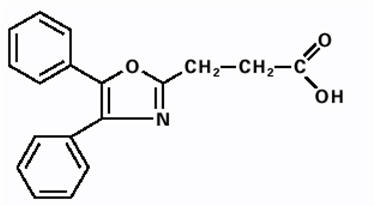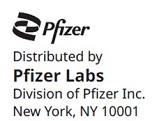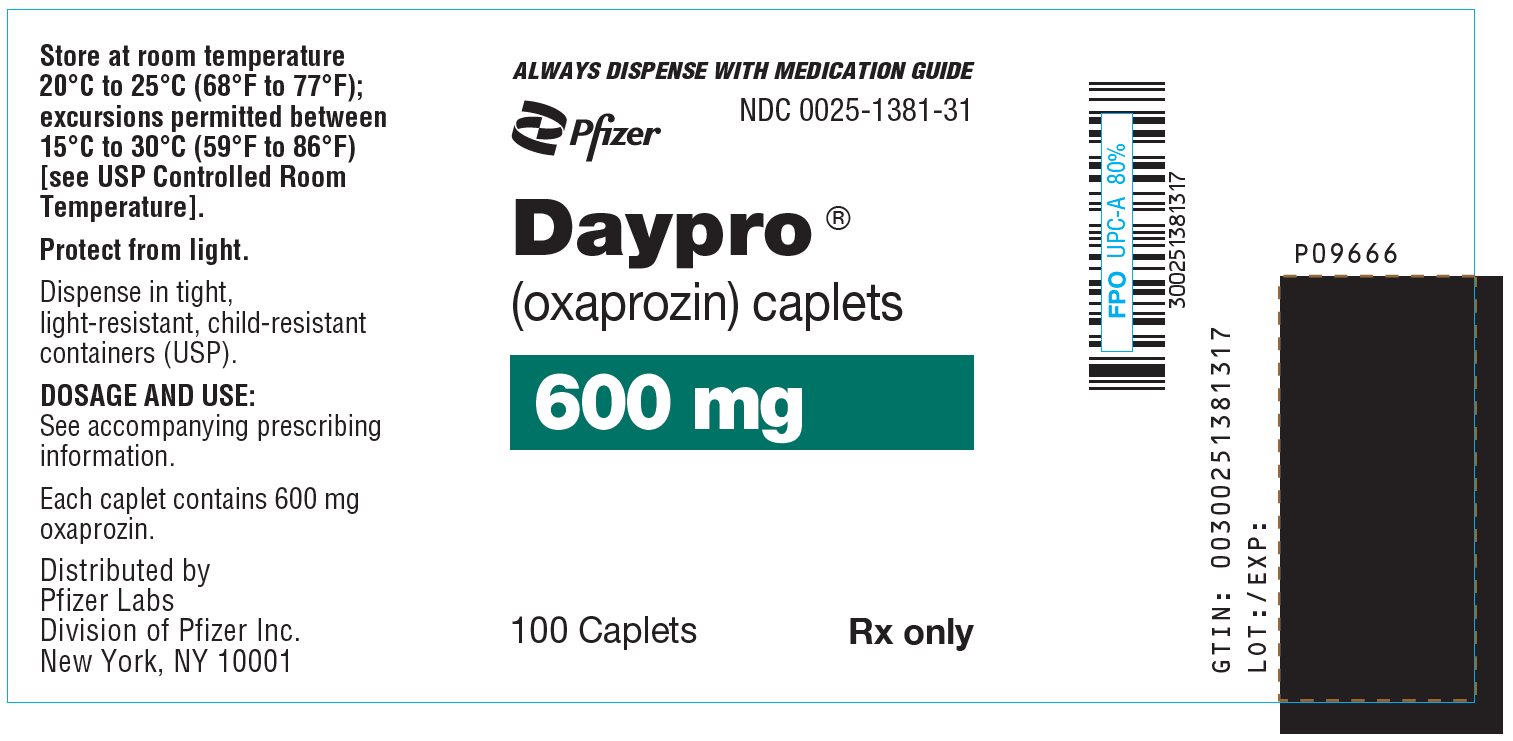 DRUG LABEL: Daypro
NDC: 0025-1381 | Form: TABLET, FILM COATED
Manufacturer: Pfizer Laboratories Div Pfizer Inc
Category: prescription | Type: HUMAN PRESCRIPTION DRUG LABEL
Date: 20251111

ACTIVE INGREDIENTS: OXAPROZIN 600 mg/1 1
INACTIVE INGREDIENTS: MICROCRYSTALLINE CELLULOSE; HYPROMELLOSE, UNSPECIFIED; METHYLCELLULOSE (100 MPA.S); MAGNESIUM STEARATE; POLACRILIN POTASSIUM; POLYETHYLENE GLYCOL, UNSPECIFIED; TITANIUM DIOXIDE

HIGHLIGHTS OF PRESCRIBING INFORMATION

These highlights do not include all the information needed to use DAYPRO safely and effectively. See full prescribing information for DAYPRO.
DAYPRO® (oxaprozin) caplets, for oral use
Initial U.S. Approval: 1992

RECENT MAJOR CHANGES

Warnings and Precautions, Serious Skin Reactions (5.9) | 11/2024

WARNING: RISK OF SERIOUS CARDIOVASCULAR AND GASTROINTESTINAL EVENTS

See full prescribing information for complete boxed warning.

- Nonsteroidal anti-inflammatory drugs (NSAIDs) cause an increased risk of serious cardiovascular thrombotic events, including myocardial infarction and stroke, which can be fatal. This risk may occur early in treatment and may increase with duration of use (5.1)
- DAYPRO is contraindicated in the setting of coronary artery bypass graft (CABG) surgery (4, 5.1)
- NSAIDs cause an increased risk of serious gastrointestinal (GI) adverse events including bleeding, ulceration, and perforation of the stomach or intestines, which can be fatal. These events can occur at any time during use and without warning symptoms. Elderly patients and patients with a prior history of peptic ulcer disease and/or GI bleeding are at greater risk for serious GI events (5.2)

1 INDICATIONS AND USAGE

DAYPRO is a non-steroidal anti-inflammatory drug indicated for:

- Relief of signs and symptoms of Osteoarthritis (OA) (1)
- Relief of signs and symptoms of Rheumatoid Arthritis (RA) (1)
- Relief of signs and symptoms of Juvenile Rheumatoid Arthritis (JRA) (1)

2 DOSAGE AND ADMINISTRATION

- Use the lowest effective dosage for shortest duration consistent with individual patient treatment goals (2.1)
- OA: 1200 mg (two 600 mg caplets) given orally once a day (2.2, 2.5, 14.1)
- RA: 1200 mg (two 600 mg caplets) given orally once a day (2.3, 2.5, 14.2)
- JRA: 600 mg once daily in patients 22–31 kg. 900 mg once daily in patients 32–54 kg. 1200 mg once daily in patients ≥55 kg (2.4, 2.5)

3 DOSAGE FORMS AND STRENGTHS

DAYPRO (oxaprozin) caplets: 600 mg (3)

4 CONTRAINDICATIONS

- Known hypersensitivity to oxaprozin or any components of the drug product (4)
- History of asthma, urticaria, or other allergic-type reactions after taking aspirin or other NSAIDs (4)
- In the setting of CABG surgery (4)

5 WARNINGS AND PRECAUTIONS

- Hepatotoxicity: Inform patients of warning signs and symptoms of hepatotoxicity. Discontinue if abnormal liver tests persist or worsen or if clinical signs and symptoms of liver disease develop (5.3)
- Hypertension: Patients taking some antihypertensive medications may have impaired response to these therapies when taking NSAIDs. Monitor blood pressure (5.4, 7)
- Heart Failure and Edema: Avoid use of DAYPRO in patients with severe heart failure unless benefits are expected to outweigh risk of worsening heart failure (5.5)
- Renal Toxicity: Monitor renal function in patients with renal or hepatic impairment, heart failure, dehydration, or hypovolemia. Avoid use of DAYPRO in patients with advanced renal disease unless benefits are expected to outweigh risk of worsening renal function (5.6)
- Anaphylactic Reactions: Seek emergency help if an anaphylactic reaction occurs (5.7)
- Exacerbation of Asthma Related to Aspirin Sensitivity: DAYPRO is contraindicated in patients with aspirin-sensitive asthma. Monitor patients with preexisting asthma (without aspirin sensitivity) (5.8)
- Serious Skin Reactions: Discontinue DAYPRO at first appearance of skin rash or other signs of hypersensitivity (5.9)
- Drug Reaction with Eosinophilia and Systemic Symptoms (DRESS): Discontinue and evaluate clinically (5.10)
- Fetal Toxicity: Limit use of NSAIDs, including DAYPRO, between about 20 to 30 weeks in pregnancy due to the risk of oligohydramnios/fetal renal dysfunction. Avoid use of NSAIDs in women at about 30 weeks gestation and later in pregnancy due to the risks of oligohydramnios/fetal renal dysfunction and premature closure of the fetal ductus arteriosus (5.11, 8.1)
- Hematologic Toxicity: Monitor hemoglobin or hematocrit in patients with any signs or symptoms of anemia (5.12, 7)

6 ADVERSE REACTIONS

Most common adverse reactions (>3%) are: constipation, diarrhea, dyspepsia, nausea, rash (6.1)

To report SUSPECTED ADVERSE REACTIONS, contact Pfizer Inc. at 1-800-438-1985 or FDA at 1-800-FDA-1088 or www.fda.gov/medwatch.

7 DRUG INTERACTIONS

- Drugs that Interfere with Hemostasis (e.g., warfarin, aspirin, selective serotonin reuptake inhibitors [SSRIs]/serotonin norepinephrine reuptake inhibitors [SNRIs]): Monitor patients for bleeding who are concomitantly taking DAYPRO with drugs that interfere with hemostasis. Concomitant use of DAYPRO and analgesic doses of aspirin is not generally recommended (7)
- Angiotensin Converting Enzyme (ACE) Inhibitors, Angiotensin Receptor Blockers (ARB), or Beta-Blockers: Concomitant use with DAYPRO may diminish the antihypertensive effect of these drugs. Monitor blood pressure (7)
- ACE Inhibitors and ARBs: Concomitant use with DAYPRO in elderly, volume depleted, or those with renal impairment may result in deterioration of renal function. In such high risk patients, monitor for signs of worsening renal function (7)
- Diuretics: NSAIDs can reduce natriuretic effect of furosemide and thiazide diuretics. Monitor patients to assure diuretic efficacy including antihypertensive effects (7)
- Digoxin: Concomitant use with DAYPRO can increase serum concentration and prolong half-life of digoxin. Monitor serum digoxin levels (7)

8 USE IN SPECIFIC POPULATIONS

Infertility: NSAIDs are associated with reversible infertility. Consider withdrawal of DAYPRO in women who have difficulties conceiving (8.3)

FULL PRESCRIBING INFORMATION

WARNING: RISK OF SERIOUS CARDIOVASCULAR AND GASTROINTESTINAL EVENTS

Cardiovascular Thrombotic Events

- Nonsteroidal anti-inflammatory drugs (NSAIDs) cause an increased risk of serious cardiovascular thrombotic events, including myocardial infarction and stroke, which can be fatal. This risk may occur early in treatment and may increase with duration of use [see Warnings and Precautions (5.1)].
- DAYPRO is contraindicated in the setting of coronary artery bypass graft (CABG) surgery [see Contraindications (4) and Warnings and Precautions (5.1)].

Gastrointestinal Bleeding, Ulceration, and Perforation

- NSAIDs cause an increased risk of serious gastrointestinal (GI) adverse events including bleeding, ulceration, and perforation of the stomach or intestines, which can be fatal. These events can occur at any time during use and without warning symptoms. Elderly patients and patients with a prior history of peptic ulcer disease and/or GI bleeding are at greater risk for serious GI events [see Warnings and Precautions (5.2)].

1 INDICATIONS AND USAGE

DAYPRO is indicated:

- For relief of the signs and symptoms of osteoarthritis
- For relief of the signs and symptoms of rheumatoid arthritis
- For relief of the signs and symptoms of juvenile rheumatoid arthritis

2 DOSAGE AND ADMINISTRATION

2.1 General Dosing Instructions

Carefully consider the potential benefits and risks of DAYPRO and other treatment options before deciding to use DAYPRO. Use the lowest effective dosage for the shortest duration consistent with individual patient treatment goals [see Warnings and Precautions (5)].

2.2 Osteoarthritis

For OA, the dosage is 1200 mg (two 600 mg caplets) given orally once a day [see Dosage and Administration (2.5)].

2.3 Rheumatoid Arthritis

For RA, the dosage is 1200 mg (two 600 mg caplets) given orally once a day [see Dosage and Administration (2.5)].

2.4 Juvenile Rheumatoid Arthritis

For JRA, in patients 6 to 16 years of age, the recommended dosage given orally once per day should be based on body weight of the patient as given in Table 1 [see Dosage and Administration (2.5)].

Table 1. Recommended Daily Dose of DAYPRO by Body Weight in Pediatric Patients
Body Weight Range (kg) | Dose (mg)
22–31 | 600
32–54 | 900
≥55 | 1200

2.5 Individualization of Dosage

After observing the response to initial therapy with DAYPRO, the dose and frequency should be adjusted to suit an individual patient's needs. In osteoarthritis and rheumatoid arthritis and juvenile rheumatoid arthritis, the dosage should be individualized to the lowest effective dose of DAYPRO to minimize adverse effects. The maximum recommended total daily dose of DAYPRO in adults is 1800 mg (26 mg/kg, whichever is lower) in divided doses. In children, doses greater than 1200 mg have not been studied.

Patients with low body weight should initiate therapy with 600 mg once daily. Patients with severe renal impairment or on dialysis should also initiate therapy with 600 mg once daily. If there is insufficient relief of symptoms in such patients, the dose may be cautiously increased to 1200 mg, but only with close monitoring [see Clinical Pharmacology (12.3)].

In adults, in cases where a quick onset of action is important, the pharmacokinetics of oxaprozin allows therapy to be started with a one-time loading dose of 1200 mg to 1800 mg (not to exceed 26 mg/kg). Doses larger than 1200 mg/day on a chronic basis should be reserved for patients who weigh more than 50 kg, have normal renal and hepatic function, are at low risk of peptic ulcer, and whose severity of disease justifies maximal therapy. Physicians should ensure that patients are tolerating doses in the 600 mg to 1200 mg/day range without gastroenterologic, renal, hepatic, or dermatologic adverse effects before advancing to the larger doses. Most patients will tolerate once-a-day dosing with DAYPRO, although divided doses may be tried in patients unable to tolerate single doses.

3 DOSAGE FORMS AND STRENGTHS

DAYPRO (oxaprozin) caplets: 600 mg caplets, white, capsule-shaped, scored, film-coated, with DAYPRO debossed on one side and 1381 on the other side.

4 CONTRAINDICATIONS

DAYPRO is contraindicated in the following patients:

- Known hypersensitivity (e.g., anaphylactic reactions and serious skin reactions) to oxaprozin or any components of the drug product [see Warnings and Precautions (5.7, 5.9)]
- History of asthma, urticaria, or other allergic-type reactions after taking aspirin or other NSAIDs. Severe, sometimes fatal, anaphylactic reactions to NSAIDs have been reported in such patients [see Warnings and Precautions (5.7, 5.8)]
- In the setting of CABG surgery [see Warnings and Precautions (5.1)]

5 WARNINGS AND PRECAUTIONS

5.1 Cardiovascular Thrombotic Events

Clinical trials of several cyclooxygenase-2 (COX-2) selective and nonselective NSAIDs of up to three years duration have shown an increased risk of serious cardiovascular (CV) thrombotic events, including myocardial infarction (MI) and stroke, which can be fatal. Based on available data, it is unclear that the risk for CV thrombotic events is similar for all NSAIDs. The relative increase in serious CV thrombotic events over baseline conferred by NSAID use appears to be similar in those with and without known CV disease or risk factors for CV disease. However, patients with known CV disease or risk factors had a higher absolute incidence of excess serious CV thrombotic events, due to their increased baseline rate. Some observational studies found that this increased risk of serious CV thrombotic events began as early as the first weeks of treatment. The increase in CV thrombotic risk has been observed most consistently at higher doses.

To minimize the potential risk for an adverse CV event in NSAID-treated patients, use the lowest effective dose for the shortest duration possible. Physicians and patients should remain alert for the development of such events, throughout the entire treatment course, even in the absence of previous CV symptoms. Patients should be informed about the symptoms of serious CV events and the steps to take if they occur.

There is no consistent evidence that concurrent use of aspirin mitigates the increased risk of serious CV thrombotic events associated with NSAID use. The concurrent use of aspirin and an NSAID, such as oxaprozin, increases the risk of serious gastrointestinal (GI) events [see Warnings and Precautions (5.2)].

Status Post Coronary Artery Bypass Graft (CABG) Surgery

Two large, controlled clinical trials of a COX-2 selective NSAID for the treatment of pain in the first 10 to 14 days following CABG surgery found an increased incidence of myocardial infarction and stroke. NSAIDs are contraindicated in the setting of CABG [see Contraindications (4)].

Post-MI Patients

Observational studies conducted in the Danish National Registry have demonstrated that patients treated with NSAIDs in the post-MI period were at increased risk of reinfarction, CV-related death, and all-cause mortality beginning in the first week of treatment. In this same cohort, the incidence of death in the first year post-MI was 20 per 100 person years in NSAID-treated patients compared to 12 per 100 person years in non-NSAID exposed patients. Although the absolute rate of death declined somewhat after the first year post-MI, the increased relative risk of death in NSAID users persisted over at least the next four years of follow-up.

Avoid the use of DAYPRO in patients with a recent MI unless the benefits are expected to outweigh the risk of recurrent CV thrombotic events. If DAYPRO is used in patients with a recent MI, monitor patients for signs of cardiac ischemia.

5.2 Gastrointestinal Bleeding, Ulceration, and Perforation

NSAIDs, including DAYPRO, cause serious gastrointestinal (GI) adverse events including inflammation, bleeding, ulceration, and perforation of the esophagus, stomach, small intestine, or large intestine, which can be fatal. These serious adverse events can occur at any time, with or without warning symptoms, in patients treated with NSAIDs. Only one in five patients, who develop a serious upper GI adverse event on NSAID therapy, is symptomatic. Upper GI ulcers, gross bleeding, or perforation caused by NSAIDs occurred in approximately 1% of patients treated for 3 to 6 months, and in about 2% to 4% of patients treated for one year. However, even short-term NSAID therapy is not without risk.

Risk Factors for GI Bleeding, Ulceration, and Perforation

Patients with a prior history of peptic ulcer disease and/or GI bleeding who used NSAIDs had a greater than 10-times increased risk for developing a GI bleed compared to patients without these risk factors. Other factors that increase the risk of GI bleeding in patients treated with NSAIDs include longer duration of NSAID therapy; concomitant use of oral corticosteroids, antiplatelet drugs (such as aspirin), anticoagulants, or selective serotonin reuptake inhibitors (SSRIs); smoking; use of alcohol; older age; and poor general health status. Most postmarketing reports of fatal GI events occurred in elderly or debilitated patients. Additionally, patients with advanced liver disease and/or coagulopathy are at increased risk for GI bleeding.

Strategies to Minimize the GI Risks in NSAID-treated patients:

- Use the lowest effective dosage for the shortest possible duration.
- Avoid administration of more than one NSAID at a time.
- Avoid use in patients at higher risk unless benefits are expected to outweigh the increased risk of bleeding. For such patients, as well as those with active GI bleeding, consider alternate therapies other than NSAIDs.
- Remain alert for signs and symptoms of GI ulceration and bleeding during NSAID therapy.
- If a serious GI adverse event is suspected, promptly initiate evaluation and treatment, and discontinue DAYPRO until a serious GI adverse event is ruled out.
- In the setting of concomitant use of low-dose aspirin for cardiac prophylaxis, monitor patients more closely for evidence of GI bleeding [see Drug Interactions (7)].

5.3 Hepatotoxicity

Elevations of alanine aminotransferase (ALT) or aspartate aminotransferase (AST) (three or more times the upper limit of normal [ULN]) have been reported in approximately 1% of NSAID-treated patients in clinical trials. In addition, rare, sometimes fatal, cases of severe hepatic injury, including fulminant hepatitis, liver necrosis, and hepatic failure have been reported.

Elevations of ALT or AST (less than three times ULN) may occur in up to 15% of patients treated with NSAIDs including oxaprozin.

Inform patients of the warning signs and symptoms of hepatotoxicity (e.g., nausea, fatigue, lethargy, diarrhea, pruritus, jaundice, right upper quadrant tenderness, and "flu-like" symptoms). If clinical signs and symptoms consistent with liver disease develop, or if systemic manifestations occur (e.g., eosinophilia, rash), discontinue DAYPRO immediately, and perform a clinical evaluation of the patient.

5.4 Hypertension

NSAIDs, including DAYPRO, can lead to new onset of hypertension or worsening of preexisting hypertension, either of which may contribute to the increased incidence of CV events. Patients taking angiotensin converting enzyme (ACE) inhibitors, thiazide diuretics, or loop diuretics may have impaired response to these therapies when taking NSAIDs [see Drug Interactions (7)].

Monitor blood pressure (BP) during the initiation of NSAID treatment and throughout the course of therapy.

5.5 Heart Failure and Edema

The Coxib and traditional NSAID Trialists' Collaboration meta-analysis of randomized controlled trials demonstrated an approximately two-fold increase in hospitalizations for heart failure in COX-2 selective-treated patients and nonselective NSAID-treated patients compared to placebo-treated patients. In a Danish National Registry study of patients with heart failure, NSAID use increased the risk of MI, hospitalization for heart failure, and death.

Additionally, fluid retention and edema have been observed in some patients treated with NSAIDs. Use of oxaprozin may blunt the CV effects of several therapeutic agents used to treat these medical conditions (e.g., diuretics, ACE inhibitors, or angiotensin receptor blockers [ARBs]) [see Drug Interactions (7)].

Avoid the use of DAYPRO in patients with severe heart failure unless the benefits are expected to outweigh the risk of worsening heart failure. If DAYPRO is used in patients with severe heart failure, monitor patients for signs of worsening heart failure.

5.6 Renal Toxicity and Hyperkalemia

Renal Toxicity

Long-term administration of NSAIDs has resulted in renal papillary necrosis and other renal injury.

Renal toxicity has also been seen in patients in whom renal prostaglandins have a compensatory role in the maintenance of renal perfusion. In these patients, administration of an NSAID may cause a dose-dependent reduction in prostaglandin formation and, secondarily, in renal blood flow, which may precipitate overt renal decompensation. Patients at greatest risk of this reaction are those with impaired renal function, dehydration, hypovolemia, heart failure, liver dysfunction, those taking diuretics and ACE inhibitors or ARBs, and the elderly. Discontinuation of NSAID therapy is usually followed by recovery to the pretreatment state.

No information is available from controlled clinical studies regarding the use of DAYPRO in patients with advanced renal disease. The renal effects of DAYPRO may hasten the progression of renal dysfunction in patients with preexisting renal disease.

Correct volume status in dehydrated or hypovolemic patients prior to initiating DAYPRO. Monitor renal function in patients with renal or hepatic impairment, heart failure, dehydration, or hypovolemia during use of DAYPRO [see Drug Interactions (7)]. Avoid the use of DAYPRO in patients with advanced renal disease unless the benefits are expected to outweigh the risk of worsening renal function. If DAYPRO is used in patients with advanced renal disease, monitor patients for signs of worsening renal function.

Hyperkalemia

Increases in serum potassium concentration, including hyperkalemia, have been reported with use of NSAIDs even in some patients without renal impairment. In patients with normal renal function, these effects have been attributed to a hyporeninemic-hypoaldosteronism state.

5.7 Anaphylactic Reactions

Oxaprozin has been associated with anaphylactic reactions in patients with and without known hypersensitivity to oxaprozin and in patients with aspirin-sensitive asthma [see Contraindications (4) and Warnings and Precautions (5.8)].

Seek emergency help if an anaphylactic reaction occurs.

5.8 Exacerbation of Asthma Related to Aspirin Sensitivity

A subpopulation of patients with asthma may have aspirin-sensitive asthma which may include chronic rhinosinusitis complicated by nasal polyps; severe, potentially fatal bronchospasm; and/or intolerance to aspirin and other NSAIDs. Because cross-reactivity between aspirin and other NSAIDs has been reported in such aspirin-sensitive patients, DAYPRO is contraindicated in patients with this form of aspirin sensitivity [see Contraindications (4)]. When DAYPRO is used in patients with preexisting asthma (without known aspirin sensitivity), monitor patients for changes in the signs and symptoms of asthma.

5.9 Serious Skin Reactions

NSAIDs, including oxaprozin, can cause serious skin adverse reactions such as exfoliative dermatitis, Stevens-Johnson Syndrome (SJS), and toxic epidermal necrolysis (TEN), which can be fatal. NSAIDs can also cause fixed drug eruption (FDE). FDE may present as a more severe variant known as generalized bullous fixed drug eruption (GBFDE), which can be life-threatening. These serious events may occur without warning. Inform patients about the signs and symptoms of serious skin reactions, and to discontinue the use of DAYPRO at the first appearance of skin rash or any other sign of hypersensitivity. DAYPRO is contraindicated in patients with previous serious skin reactions to NSAIDs [see Contraindications (4)].

5.10 Drug Reaction with Eosinophilia and Systemic Symptoms (DRESS)

Drug Reaction with Eosinophilia and Systemic Symptoms (DRESS) has been reported in patients taking NSAIDs such as DAYPRO. Some of these events have been fatal or life-threatening. DRESS typically, although not exclusively, presents with fever, rash, lymphadenopathy, and/or facial swelling. Other clinical manifestations may include hepatitis, nephritis, hematological abnormalities, myocarditis, or myositis. Sometimes symptoms of DRESS may resemble an acute viral infection. Eosinophilia is often present. Because this disorder is variable in its presentation, other organ systems not noted here may be involved. It is important to note that early manifestations of hypersensitivity, such as fever or lymphadenopathy, may be present even though rash is not evident. If such signs or symptoms are present, discontinue DAYPRO and evaluate the patient immediately.

5.11 Fetal Toxicity

Premature Closure of Fetal Ductus Arteriosus

Avoid use of NSAIDs, including DAYPRO, in pregnant women at about 30 weeks gestation and later. NSAIDs, including DAYPRO, increase the risk of premature closure of the fetal ductus arteriosus at approximately this gestational age.

Oligohydramnios/Neonatal Renal Impairment

Use of NSAIDs, including DAYPRO, at about 20 weeks gestation or later in pregnancy may cause fetal renal dysfunction leading to oligohydramnios and, in some cases, neonatal renal impairment. These adverse outcomes are seen, on average, after days to weeks of treatment, although oligohydramnios has been infrequently reported as soon as 48 hours after NSAID initiation. Oligohydramnios is often, but not always, reversible with treatment discontinuation. Complications of prolonged oligohydramnios may, for example, include limb contractures and delayed lung maturation. In some postmarketing cases of impaired neonatal renal function, invasive procedures such as exchange transfusion or dialysis were required.

If NSAID treatment is necessary between about 20 weeks and 30 weeks gestation, limit DAYPRO use to the lowest effective dose and shortest duration possible. Consider ultrasound monitoring of amniotic fluid if DAYPRO treatment extends beyond 48 hours. Discontinue DAYPRO if oligohydramnios occurs and follow up according to clinical practice [see Use in Specific Populations (8.1)].

5.12 Hematologic Toxicity

Anemia has occurred in NSAID-treated patients. This may be due to occult or gross blood loss, fluid retention, or an incompletely described effect on erythropoiesis. If a patient treated with DAYPRO has any signs or symptoms of anemia, monitor hemoglobin or hematocrit.

NSAIDs, including DAYPRO, may increase the risk of bleeding events. Co-morbid conditions such as coagulation disorders or concomitant use of warfarin, other anticoagulants, antiplatelet drugs (e.g., aspirin), SSRIs, and serotonin norepinephrine reuptake inhibitors (SNRIs) may increase this risk. Monitor these patients for signs of bleeding [see Drug Interactions (7)].

5.13 Masking of Inflammation and Fever

The pharmacological activity of DAYPRO in reducing inflammation, and possibly fever, may diminish the utility of diagnostic signs in detecting infections.

5.14 Laboratory Monitoring

Because serious GI bleeding, hepatotoxicity, and renal injury can occur without warning symptoms or signs, consider monitoring patients on long-term NSAID treatment with a complete blood count (CBC) and a chemistry profile periodically [see Warnings and Precautions (5.2, 5.3, 5.6)].

5.15 Photosensitivity

Oxaprozin has been associated with rash and/or mild photosensitivity in dermatologic testing. An increased incidence of rash on sun-exposed skin was seen in some patients in the clinical trials.

6 ADVERSE REACTIONS

The following adverse reactions are discussed in greater detail in other sections of the labeling:

- Cardiovascular Thrombotic Events [see Warnings and Precautions (5.1)]
- GI Bleeding, Ulceration and Perforation [see Warnings and Precautions (5.2)]
- Hepatotoxicity [see Warnings and Precautions (5.3)]
- Hypertension [see Warnings and Precautions (5.4)]
- Heart Failure and Edema [see Warnings and Precautions (5.5)]
- Renal Toxicity and Hyperkalemia [see Warnings and Precautions (5.6)]
- Anaphylactic Reactions [see Warnings and Precautions (5.7)]
- Serious Skin Reactions [see Warnings and Precautions (5.9)]
- Hematologic Toxicity [see Warnings and Precautions (5.12)]

6.1 Clinical Trials Experience

Because clinical trials are conducted under widely varying conditions, adverse reaction rates observed in the clinical trials of a drug cannot be directly compared to rates in the clinical trials of another drug and may not reflect the rates observed in practice.

Adverse reaction data were derived from patients who received DAYPRO in multidose, controlled, and open-label clinical trials. Rates for events from clinical trial experience are based on 2253 patients who took 1200 mg to 1800 mg DAYPRO per day in clinical trials. Of these, 1721 patients were treated for at least 1 month, 971 patients for at least 3 months, and 366 patients for more than 1 year.

Incidence Greater than 1%: In clinical trials of DAYPRO or in patients taking other NSAIDs, the following adverse reactions occurred at an incidence greater than 1%.

Cardiovascular system: edema.

Digestive system: abdominal pain/distress, anorexia, constipation, diarrhea, dyspepsia, flatulence, gastrointestinal ulcers (gastric/duodenal), gross bleeding/perforation, heartburn, liver enzyme elevations, nausea, vomiting.

Hematologic system: anemia, increased bleeding time.

Nervous system: CNS inhibition (depression, sedation, somnolence, or confusion), disturbance of sleep, dizziness, headache.

Skin and appendages: pruritus, rash.

Special senses: tinnitus.

Urogenital system: abnormal renal function, dysuria or frequency.

Incidence Greater than 1%: The following adverse reactions were reported in clinical trials or in patients taking other NSAIDs.

Body as a whole: appetite changes, death, drug hypersensitivity reactions including anaphylaxis, fever, infection, sepsis.

Cardiovascular system: arrhythmia, blood pressure changes, congestive heart failure, hypertension, hypotension, myocardial infarction, palpitations, tachycardia, syncope, vasculitis.

Digestive system: alteration in taste, dry mouth, eructation, esophagitis, gastritis, glossitis, hematemesis, jaundice, liver function abnormalities including liver failure, stomatitis, hemorrhoidal or rectal bleeding.

Hematologic system: aplastic anemia, ecchymoses, eosinophilia, hemolytic anemia, lymphadenopathy, melena, purpura, thrombocytopenia, leukopenia.

Metabolic system: hyperglycemia, weight changes.

Nervous system: anxiety, asthenia, coma, convulsions, dream abnormalities, drowsiness, hallucinations, insomnia, malaise, meningitis, nervousness, paresthesia, tremors, vertigo, weakness.

Respiratory system: asthma, dyspnea, pulmonary infections, pneumonia, sinusitis, symptoms of upper respiratory tract infection, respiratory depression.

Skin: alopecia, angioedema, urticaria, photosensitivity, sweat.

Special senses: blurred vision, conjunctivitis, hearing decrease.

Urogenital: cystitis, hematuria, increase in menstrual flow, oliguria/ polyuria, proteinuria, renal insufficiency, decreased menstrual flow.

6.2 Postmarketing Experience

The following adverse reactions have been identified during post approval use of DAYPRO. Because these reactions are reported voluntarily from a population of uncertain size, it is not always possible to reliably estimate their frequency or establish a causal relationship to drug exposure.

Body as a whole: serum sickness.

Digestive system: hepatitis, pancreatitis.

Hematologic system: agranulocytosis, pancytopenia.

Skin: pseudoporphyria, exfoliative dermatitis, erythema multiforme, Stevens-Johnson Syndrome, fixed drug eruption (FDE), toxic epidermal necrolysis (Lyell's syndrome).

Urogenital: acute interstitial nephritis, nephrotic syndrome, acute renal failure.

7 DRUG INTERACTIONS

See Table 2 for clinically significant drug interactions with oxaprozin [see Clinical Pharmacology (12.3)].

Table 2: Clinically Significant Drug Interactions with Oxaprozin
Drugs That Interfere with Hemostasis
Clinical Impact: | - Oxaprozin and anticoagulants such as warfarin have a synergistic effect on bleeding. The concomitant use of oxaprozin and anticoagulants have an increased risk of serious bleeding compared to the use of either drug alone. - Serotonin release by platelets plays an important role in hemostasis. Case-control and cohort epidemiological studies showed that concomitant use of drugs that interfere with serotonin reuptake and an NSAID may potentiate the risk of bleeding more than an NSAID alone.
Intervention: | Monitor patients with concomitant use of DAYPRO with anticoagulants (e.g., warfarin), antiplatelet drugs (e.g., aspirin), SSRIs, and SNRIs for signs of bleeding [see Warnings and Precautions (5.12)].
Aspirin
Clinical Impact: | Controlled clinical studies showed that the concomitant use of NSAIDs and analgesic doses of aspirin does not produce any greater therapeutic effect than the use of NSAIDs alone. In a clinical study, the concomitant use of an NSAID and aspirin was associated with a significantly increased incidence of GI adverse reactions as compared to use of the NSAID alone [see Warnings and Precautions (5.2)].
Intervention: | Concomitant use of DAYPRO and analgesic doses of aspirin is not generally recommended because of the increased risk of bleeding [see Warnings and Precautions (5.12)].
Intervention: | DAYPRO is not a substitute for low dose aspirin for cardiovascular protection.
ACE Inhibitors, Angiotensin Receptor Blockers, and Beta-Blockers
Clinical Impact: | - NSAIDs may diminish the antihypertensive effect of ACE inhibitors, ARBs, or beta-blockers (including propranolol). - In patients who are elderly, volume-depleted (including those on diuretic therapy), or have renal impairment, co-administration of an NSAID with ACE inhibitors or ARBs may result in deterioration of renal function, including possible acute renal failure. These effects are usually reversible.
Intervention: | - During concomitant use of DAYPRO and ACE inhibitors, ARBs, or beta-blockers, monitor blood pressure to ensure that the desired blood pressure is obtained. - During concomitant use of DAYPRO and ACE inhibitors or ARBs in patients who are elderly, volume-depleted, or have impaired renal function, monitor for signs of worsening renal function [see Warnings and Precautions (5.6)]. - When these drugs are administered concomitantly, patients should be adequately hydrated. Assess renal function at the beginning of the concomitant treatment and periodically thereafter.
Diuretics
Clinical Impact: | Clinical studies, as well as post-marketing observations, showed that NSAIDs reduced the natriuretic effect of loop diuretics (e.g., furosemide) and thiazide diuretics in some patients. This effect has been attributed to the NSAID inhibition of renal prostaglandin synthesis.
Intervention: | During concomitant use of DAYPRO with diuretics, observe patients for signs of worsening renal function, in addition to assuring diuretic efficacy including antihypertensive effects [see Warnings and Precautions (5.6)].
Digoxin
Clinical Impact: | The concomitant use of oxaprozin with digoxin has been reported to increase the serum concentration and prolong the half-life of digoxin.
Intervention: | During concomitant use of DAYPRO and digoxin, monitor serum digoxin levels.
Lithium
Clinical Impact: | NSAIDs have produced elevations in plasma lithium levels and reductions in renal lithium clearance. The mean minimum lithium concentration increased 15%, and the renal clearance decreased by approximately 20%. This effect has been attributed to NSAID inhibition of renal prostaglandin synthesis.
Intervention: | During concomitant use of DAYPRO and lithium, monitor patients for signs of lithium toxicity.
Methotrexate
Clinical Impact: | Concomitant use of NSAIDs and methotrexate may increase the risk for methotrexate toxicity (e.g., neutropenia, thrombocytopenia, renal dysfunction) because NSAID administration may result in increased plasma levels of methotrexate, especially in patients receiving high doses of methotrexate.
Intervention: | During concomitant use of DAYPRO and methotrexate, monitor patients for methotrexate toxicity.
Cyclosporine
Clinical Impact: | Concomitant use of DAYPRO and cyclosporine may increase cyclosporine's nephrotoxicity.
Intervention: | During concomitant use of DAYPRO and cyclosporine, monitor patients for signs of worsening renal function.
NSAIDs and Salicylates
Clinical Impact: | Concomitant use of oxaprozin with other NSAIDs or salicylates (e.g., diflunisal, salsalate) increases the risk of GI toxicity, with little or no increase in efficacy [see Warnings and Precautions (5.2)].
Intervention: | The concomitant use of oxaprozin with other NSAIDs or salicylates is not recommended.
Pemetrexed
Clinical Impact: | Concomitant use of DAYPRO and pemetrexed may increase the risk of pemetrexed-associated myelosuppression, renal, and GI toxicity (see the pemetrexed prescribing information).
Intervention: | During concomitant use of DAYPRO and pemetrexed, in patients with renal impairment whose creatinine clearance ranges from 45 to 79 mL/min, monitor for myelosuppression, renal and GI toxicity.
Intervention: | NSAIDs with short elimination half-lives (e.g., diclofenac, indomethacin) should be avoided for a period of two days before, the day of, and two days following administration of pemetrexed.
Intervention: | In the absence of data regarding potential interaction between pemetrexed and NSAIDs with longer half-lives (e.g., meloxicam, nabumetone), patients taking these NSAIDs should interrupt dosing for at least five days before, the day of, and two days following pemetrexed administration.
Corticosteroids
Clinical Impact: | Concomitant use of corticosteroids with DAYPRO may increase the risk of GI ulceration or bleeding.
Intervention: | Monitor patients with concomitant use of DAYPRO with corticosteroids for signs of bleeding [see Warnings and Precautions (5.2)].
Glyburide
Clinical Impact: | While oxaprozin does alter the pharmacokinetics of glyburide, coadministration of oxaprozin to type II non-insulin dependent diabetic patients did not affect the area under the glucose concentration curve nor the magnitude or duration of control.
Intervention: | During concomitant use of DAYPRO and glyburide, monitor patient's blood glucose in the beginning phase of cotherapy.

Laboratory Test Interactions

False-positive urine immunoassay screening tests for benzodiazepines have been reported in patients taking DAYPRO. This is due to lack of specificity of the screening tests. False-positive test results may be expected for several days following discontinuation of DAYPRO therapy. Confirmatory tests, such as gas chromatography/mass spectrometry, will distinguish DAYPRO from benzodiazepines.

8 USE IN SPECIFIC POPULATIONS

8.1 Pregnancy

Risk Summary

Use of NSAIDs, including DAYPRO, can cause premature closure of the fetal ductus arteriosus and fetal renal dysfunction leading to oligohydramnios and, in some cases, neonatal renal impairment. Because of these risks, limit dose and duration of DAYPRO use between about 20 and 30 weeks of gestation, and avoid DAYPRO use at about 30 weeks of gestation and later in pregnancy (see Clinical Considerations, Data).

Premature Closure of Fetal Ductus Arteriosus

Use of NSAIDs, including DAYPRO, at about 30 weeks gestation or later in pregnancy increases the risk of premature closure of the fetal ductus arteriosus.

Oligohydramnios/Neonatal Renal Impairment

Use of NSAIDs at about 20 weeks gestation or later in pregnancy has been associated with cases of fetal renal dysfunction leading to oligohydramnios, and in some cases, neonatal renal impairment.

Data from observational studies regarding other potential embryofetal risks of NSAID use in women in the first or second trimesters of pregnancy are inconclusive. In animal reproduction studies, oral administration of oxaprozin to pregnant rabbits at doses 0.1-times the maximum daily human dose (based on body surface area) resulted in evidence of teratogenicity; however, oral administration of oxaprozin to pregnant mice and rats during organogenesis at doses equivalent to the maximum recommended human dose revealed no evidence of teratogenicity or embryotoxicity. In rat reproduction studies in which oxaprozin was administered through late gestation failure to deliver and a reduction in live birth index was observed at doses equivalent to the maximum recommended human dose. Based on animal data, prostaglandins have been shown to have an important role in endometrial vascular permeability, blastocyst implantation, and decidualization. In animal studies, administration of prostaglandin synthesis inhibitors such as oxaprozin, resulted in increased pre- and post-implantation loss. Prostaglandins also have been shown to have an important role in fetal kidney development. In published animal studies, prostaglandin synthesis inhibitors have been reported to impair kidney development when administered at clinically relevant doses.

The estimated background risk of major birth defects and miscarriage for the indicated population(s) is unknown. All pregnancies have a background risk of birth defect, loss, or other adverse outcomes. In the U.S. general population, the estimated background risk of major birth defects and miscarriage in clinically recognized pregnancies is 2% to 4% and 15% to 20%, respectively.

Clinical Considerations

Fetal/Neonatal Adverse Reactions

Premature Closure of Fetal Ductus Arteriosus:

Avoid use of NSAIDs in women at about 30 weeks gestation and later in pregnancy, because NSAIDs, including DAYPRO, can cause premature closure of the fetal ductus arteriosus (see Data).

Oligohydramnios/Neonatal Renal Impairment:

If an NSAID is necessary at about 20 weeks gestation or later in pregnancy, limit the use to the lowest effective dose and shortest duration possible. If DAYPRO treatment extends beyond 48 hours, consider monitoring with ultrasound for oligohydramnios. If oligohydramnios occurs, discontinue DAYPRO and follow up according to clinical practice (see Data).

Labor or Delivery

There are no studies on the effects of DAYPRO during labor or delivery. In animal studies, NSAIDS, including oxaprozin, inhibit prostaglandin synthesis, cause delayed parturition, and increase the incidence of stillbirth.

Data

Human Data

Premature Closure of Fetal Ductus Arteriosus:

Published literature reports that the use of NSAIDs at about 30 weeks of gestation and later in pregnancy may cause premature closure of the fetal ductus arteriosus.

Oligohydramnios/Neonatal Renal Impairment:

Published studies and postmarketing reports describe maternal NSAID use at about 20 weeks gestation or later in pregnancy associated with fetal renal dysfunction leading to oligohydramnios, and in some cases, neonatal renal impairment. These adverse outcomes are seen, on average, after days to weeks of treatment, although oligohydramnios has been infrequently reported as soon as 48 hours after NSAID initiation. In many cases, but not all, the decrease in amniotic fluid was transient and reversible with cessation of the drug. There have been a limited number of case reports of maternal NSAID use and neonatal renal dysfunction without oligohydramnios, some of which were irreversible. Some cases of neonatal renal dysfunction required treatment with invasive procedures, such as exchange transfusion or dialysis.

Methodological limitations of these postmarketing studies and reports include lack of a control group; limited information regarding dose, duration, and timing of drug exposure; and concomitant use of other medications. These limitations preclude establishing a reliable estimate of the risk of adverse fetal and neonatal outcomes with maternal NSAID use. Because the published safety data on neonatal outcomes involved mostly preterm infants, the generalizability of certain reported risks to the full-term infant exposed to NSAIDs through maternal use is uncertain.

Animal data

Teratology studies with oxaprozin were performed in mice, rats, and rabbits in pregnant animals administered oral doses up to 200 mg/kg/day, 200 mg/kg/day, and 30 mg/kg/day, respectively, during the period of organogenesis. In rabbits, malformations were observed at doses greater than or equal to 7.5 mg/kg/day of oxaprozin (0.1 times the maximum recommended human daily dose [MRHD] of 1800 mg based on body surface area). However, in mice and rats, no drug-related developmental abnormalities or embryo-fetal toxicity were observed at doses up to 50 and 200 mg/kg/day of oxaprozin, respectively (0.1 times and 1.1 times the maximum recommended human daily dose of 1800 mg based on a body surface area comparison, respectively).

In fertility/reproductive studies in rats, 200 mg/kg/day oxaprozin was orally administered to female rats for 14 days prior to mating through lactation day (LD) 2, or from gestation day (GD) 15 through LD 2 and the females were mated with males treated with 200 mg/kg/day oxaprozin for 60 days prior to mating. Oxaprozin administration resulted in failure to deliver and a reduction in live birth index at 200 mg/kg/day (1.1-times the maximum recommended human daily dose of 1800 mg based on a body surface area comparison).

8.2 Lactation

Risk Summary

Lactation studies have not been conducted with DAYPRO. It is not known whether DAYPRO is excreted in human milk. DAYPRO should be administered to lactating women only if clearly indicated. The developmental and health benefits of breastfeeding should be considered along with the mother's clinical need for DAYPRO and any potential adverse effects on the breastfed infant from the DAYPRO or from the underlying maternal condition.

8.3 Females and Males of Reproductive Potential

Infertility

Females

Based on the mechanism of action, the use of prostaglandin-mediated NSAIDs, including DAYPRO, may delay or prevent rupture of ovarian follicles, which has been associated with reversible infertility in some women. Published animal studies have shown that administration of prostaglandin synthesis inhibitors has the potential to disrupt prostaglandin-mediated follicular rupture required for ovulation. Small studies in women treated with NSAIDs have also shown a reversible delay in ovulation. Consider withdrawal of NSAIDs, including DAYPRO, in women who have difficulties conceiving or who are undergoing investigation of infertility.

Males

Testicular degeneration was observed in beagle dogs treated with 37.5 mg/kg/day (0.7-times the maximum recommended human daily dose based on body surface area) of oxaprozin for 42 days or 6 months [see Nonclinical Toxicology (13.1)]

8.4 Pediatric Use

Safety and effectiveness of DAYPRO in pediatric patients below the age of 6 years of age have not been established. The effectiveness of DAYPRO for the treatment of the signs and symptoms of juvenile rheumatoid arthritis (JRA) in pediatric patients aged 6 to 16 years is supported by evidence from adequate and well controlled studies in adult rheumatoid arthritis patients, and is based on an extrapolation of the demonstrated efficacy of DAYPRO in adults with rheumatoid arthritis and the similarity in the course of the disease and the drug's mechanism of effect between these two patient populations. Use of DAYPRO in JRA patients 6 to 16 years of age is also supported by the following pediatric studies.

The pharmacokinetic profile and tolerability of oxaprozin were assessed in JRA patients relative to adult rheumatoid arthritis patients in a 14 day multiple dose pharmacokinetic study. Apparent clearance of unbound oxaprozin in JRA patients was reduced compared to adult rheumatoid arthritis patients, but this reduction could be accounted for by differences in body weight [see Clinical Pharmacology (12.3)]. No pharmacokinetic data are available for pediatric patients under 6 years. Adverse events were reported by approximately 45% of JRA patients versus an approximate 30% incidence of adverse events in the adult rheumatoid arthritis patient cohort. Most of the adverse events were related to the gastrointestinal tract and were mild to moderate.

In a 3 month open label study, 10 to 20 mg/kg/day of oxaprozin were administered to 59 JRA patients. Adverse events were reported by 58% of JRA patients. Most of those reported were generally mild to moderate, tolerated by the patients, and did not interfere with continuing treatment. Gastrointestinal symptoms were the most frequently reported adverse effects and occurred at a higher incidence than those historically seen in controlled studies in adults. Fifty-two patients completed 3 months of treatment with a mean daily dose of 20 mg/kg. Of 30 patients who continued treatment (19 to 48 week range total treatment duration), nine (30%) experienced rash on sun-exposed areas of the skin and 5 of those discontinued treatment. Controlled clinical trials with oxaprozin in pediatric patients have not been conducted.

8.5 Geriatric Use

Elderly patients, compared to younger patients, are at greater risk for NSAID-associated serious cardiovascular, gastrointestinal, and/or renal adverse reactions. If the anticipated benefit for the elderly patient outweighs these potential risks, start dosing at the low end of the dosing range, and monitor patients for adverse effects [see Warnings and Precautions (5.1, 5.2, 5.3, 5.6, 5.14)].

No adjustment of the dose of DAYPRO is necessary in the elderly, although many elderly may need to receive a reduced dose because of low body weight or disorders associated with aging [see Clinical Pharmacology (12.3)].

Of the total number of subjects evaluated in four placebo controlled clinical studies of oxaprozin, 39% were 65 and over, and 11% were 75 and over. No overall differences in safety or effectiveness were observed between these subjects and younger subjects, and other reported clinical experience has not identified differences in responses between the elderly and younger patients, but greater sensitivity of some older individuals cannot be ruled out. Although selected elderly patients in controlled clinical trials tolerated oxaprozin as well as younger patients, caution should be exercised in treating the elderly.

DAYPRO is substantially excreted by the kidney, and the risk of toxic reactions to DAYPRO may be greater in patients with impaired renal function. Because elderly patients are more likely to have decreased renal function, care should be taken in dose selection, and it may be useful to monitor renal function [see Warnings and Precautions (5.6)].

10 OVERDOSAGE

Symptoms following acute NSAID overdosages have been typically limited to lethargy, drowsiness, nausea, vomiting, and epigastric pain, which have been generally reversible with supportive care. Gastrointestinal bleeding has occurred. Hypertension, acute renal failure, respiratory depression, and coma have occurred, but were rare [see Warnings and Precautions (5.1, 5.2, 5.4, 5.6)].

Manage patients with symptomatic and supportive care following an acute NSAID overdosage. There are no specific antidotes. It is advisable to contact a poison control center (1-800-222-1222) to determine the latest recommendations because strategies for the management of overdose are continually evolving.

If gastric decontamination may be potentially beneficial to the patient, e.g., short time since ingestion or a large overdosage (5 to 10 times the recommended dosage), consider emesis and/or activated charcoal (60 grams to 100 grams in adults, 1 gram to 2 grams per kg of body weight in pediatric patients) and/or an osmotic cathartic in symptomatic patients. Forced diuresis, alkalinization of urine, hemodialysis, or hemoperfusion may not be useful due to high protein binding.

11 DESCRIPTION

DAYPRO (oxaprozin) caplet is a nonsteroidal anti-inflammatory drug, available as caplets of 600 mg for oral administration. The chemical name is 4,5-diphenyl-2-oxazole-propionic acid. The molecular weight is 293. Its molecular formula is C18H15NO3, and it has the following chemical structure.

Oxaprozin is a white to off-white powder with a slight odor and a melting point of 162°C to 163°C. It is slightly soluble in alcohol and insoluble in water, with an octanol/water partition coefficient of 4.8 at physiologic pH (7.4). The pKa in water is 4.3.

The inactive ingredients in DAYPRO include: microcrystalline cellulose, hypromellose, methylcellulose, magnesium stearate, polacrilin potassium, starch, polyethylene glycol and titanium dioxide. DAYPRO 600-mg caplets are white, capsule-shaped, scored, film-coated, with DAYPRO debossed on one side and 1381 on the other side.

12 CLINICAL PHARMACOLOGY

12.1 Mechanism of Action

Oxaprozin has analgesic, anti-inflammatory, and antipyretic properties.

The mechanism of action of DAYPRO, like that of other NSAIDs, is not completely understood but involves inhibition of cyclooxygenase (COX-1 and COX-2).

Oxaprozin is a potent inhibitor of prostaglandin synthesis in vitro. Oxaprozin concentrations reached during therapy have produced in vivo effects. Prostaglandins sensitize afferent nerves and potentiate the action of bradykinin in inducing pain in animal models. Prostaglandins are mediators of inflammation. Because oxaprozin is an inhibitor of prostaglandin synthesis, its mode of action may be due to a decrease of prostaglandins in peripheral tissues.

12.3 Pharmacokinetics

General Pharmacokinetic Characteristics

In dose proportionality studies utilizing 600 mg, 1200 mg, and 1800 mg doses, the pharmacokinetics of oxaprozin in healthy subjects demonstrated nonlinear kinetics of both the total and unbound drug in opposite directions, i.e., dose exposure related increase in the clearance of total drug and decrease in the clearance of the unbound drug. Decreased clearance of the unbound drug was related predominantly to a decrease in the volume of distribution of the unbound drug and not an increase in the elimination half-life. This phenomenon is considered to have minimal impact on drug accumulation upon multiple dosing. The pharmacokinetic parameters of oxaprozin in healthy subjects receiving a single dose or multiple once-daily doses of 1200 mg are presented in Table 3.

Table 3. Oxaprozin Pharmacokinetic Parameters [Mean (%CV)] (1200 mg)
 | Healthy Adults (19–78 years)
 | Total Drug |  | Unbound Drug
 | Single N=35 | Multiple N=12 | Single N=35 | Multiple N=12
Tmax (hr) | 3.09 (39) | 2.44 (40) | 3.03 (48) | 2.33 (35)
Oral Clearance (L/hr/70 kg) | 0.150 (24) | 0.301 (29) | 136 (24) | 102 (45)
Apparent Volume of Distribution at Steady State (Vd/F; L/70 kg) | 11.7 (13) | 16.7 (14) | 6230 (28) | 2420 (38)
Elimination Half-life (hr) | 54.9 (49) | 41.4 (27) | 27.8 (34) | 19.5 (15)
Tmax = time to reach the maximum plasma concentration of oxaprozin.

Absorption

DAYPRO is 95% absorbed after oral administration. Food may reduce the rate of absorption of oxaprozin, but the extent of absorption is unchanged. Antacids do not significantly affect the extent and rate of DAYPRO absorption.

Distribution

The apparent volume of distribution (Vd/F) of total oxaprozin is approximately 11 to 17 L/70 kg. Oxaprozin is 99% bound to plasma proteins, primarily to albumin. At therapeutic drug concentrations, the plasma protein binding of oxaprozin is saturable, resulting in a higher proportion of the free drug as the total drug concentration is increased. With increases in single doses or following multiple once-daily dosing, the apparent volume of distribution and clearance of total drug increased, while that of unbound drug decreased due to the effects of nonlinear protein binding.

Oxaprozin penetrates into synovial tissues of rheumatoid arthritis patients with oxaprozin concentrations 2-fold and 3-fold greater than in plasma and synovial fluid, respectively. Oxaprozin is expected to be excreted in human milk based on its physical-chemical properties; however, the amount of oxaprozin excreted in breast milk has not been evaluated.

Elimination

Metabolism

Several oxaprozin metabolites have been identified in human urine or feces.

Oxaprozin is primarily metabolized in the liver, by both microsomal oxidation (65%) and glucuronic acid conjugation (35%). Ester and ether glucuronide are the major conjugated metabolites of oxaprozin. On chronic dosing, metabolites do not accumulate in the plasma of patients with normal renal function. Concentrations of the metabolites in plasma are very low.

Oxaprozin's metabolites do not have significant pharmacologic activity. The major ester and ether glucuronide conjugated metabolites have been evaluated along with oxaprozin in receptor binding studies and in vivo animal models and have demonstrated no activity. A small amount (<5%) of active phenolic metabolites are produced, but the contribution to overall activity is limited.

Excretion

Approximately 5% of the oxaprozin dose is excreted unchanged in the urine. Sixty-five percent (65%) of the dose is excreted in the urine and 35% in the feces as metabolites. Biliary excretion of unchanged oxaprozin is a minor pathway, and enterohepatic recycling of oxaprozin is insignificant. Upon chronic dosing, the accumulation half-life is approximately 22 hours. The elimination half-life is approximately twice the accumulation half-life due to increased binding and decreased clearance at lower concentrations.

Specific Populations

Geriatric: A multiple dose study comparing the pharmacokinetics of oxaprozin (1200 mg once daily) in 20 young (21 to 44 years) adults and 20 elderly (64 to 83 years) adults did not show any statistically significant differences between age groups.

Pediatric: A population pharmacokinetic study indicated no clinically important age dependent changes in the apparent clearance of unbound oxaprozin between adult rheumatoid arthritis patients (N=40) and juvenile rheumatoid arthritis (JRA) patients (≥6 years, N=44) when adjustments were made for differences in body weight between these patient groups. The extent of protein binding of oxaprozin at various therapeutic total plasma concentrations was also similar between the adult and pediatric patient groups. Pharmacokinetic model-based estimates of daily exposure (AUC0–24) to unbound oxaprozin in JRA patients relative to adult rheumatoid arthritis patients suggest dose to body weight range relationships, as shown in Table 4.

Table 4. Dose to Body Weight Range to Achieve Similar Steady-State Exposure (AUC0–24hr) to Unbound Oxaprozin in JRA Patients Relative to 70 kg Adult Rheumatoid Arthritis Patients Administered Oxaprozin 1200 mg Once Daily [Model-based nomogram derived from unbound oxaprozin steady-state plasma concentrations in JRA patients weighing 22.1 – 42.7 kg or ≥45.0 kg administered oxaprozin 600 mg or 1200 mg once daily for 14 days, respectively.]
Dose (mg) | Body Weight Range (kg)
600 | 22 –31
900 | 32 –54
1200 | ≥ 55

Race: Pharmacokinetic differences due to race have not been identified.

Hepatic Impairment: Approximately 95% of oxaprozin is metabolized by the liver. However, patients with well-compensated cirrhosis do not require reduced doses of oxaprozin as compared to patients with normal hepatic function. Nevertheless, monitor patients with severe hepatic dysfunction for adverse reactions.

Renal Impairment: Oxaprozin's renal clearance decreased proportionally with creatinine clearance (CrCL), but since only approximately 5% of oxaprozin dose is excreted unchanged in the urine, the decrease in total body clearance becomes clinically important only in those subjects with highly decreased CrCL. Oxaprozin is not significantly removed from the blood in patients undergoing hemodialysis or continuous ambulatory peritoneal dialysis (CAPD) due to its high protein binding. Oxaprozin plasma protein binding may decrease in patients with severe renal deficiency. Dosage adjustment may be necessary in patients with renal insufficiency [see Warnings and Precautions (5.6)].

Cardiac Failure: Well-compensated cardiac failure does not affect the plasma protein binding or the pharmacokinetics of oxaprozin.

Drug Interaction Studies

ACE inhibitors (enalapril): Oxaprozin has been shown to alter the pharmacokinetics of enalapril (significant decrease in dose-adjusted AUC0–24 and Cmax) and its active metabolite enalaprilat (significant increase in dose-adjusted AUC0–24) [see Drug Interactions (7)].

Aspirin: When oxaprozin was administered with aspirin, the protein binding of oxaprozin was reduced, although the clearance of free oxaprozin was not altered. The clinical significance of this interaction is not known. An in vitro study showed that oxaprozin significantly interfered with the anti-platelet activity of aspirin [see Drug Interactions (7)].

Beta-blockers (metoprolol): Subjects receiving 1200 mg DAYPRO once daily with 100 mg metoprolol twice daily exhibited statistically significant but transient increases in sitting and standing blood pressures after 14 days [see Drug Interactions (7)].

Glyburide: Oxaprozin altered the pharmacokinetics of glyburide; however, coadministration of oxaprozin to type II non-insulin dependent diabetic patients did not affect the area under the glucose concentration curve nor the magnitude or duration of control [see Drug Interactions (7)].

H2-receptor antagonists (cimetidine, ranitidine): The total clearance of oxaprozin was reduced by 20% in subjects who concurrently received therapeutic doses of cimetidine or ranitidine; no other pharmacokinetic parameter was affected. A change of clearance of this magnitude lies within the range of normal variation and is unlikely to produce a clinically detectable difference in the outcome of therapy.

Lithium: Oxaprozin has produced an elevation in plasma lithium levels and a reduction in renal lithium clearance. The mean minimum lithium concentration increased 15%, and the renal clearance decreased by approximately 20% [see Drug Interactions (7)].

Methotrexate: Coadministration of oxaprozin with methotrexate resulted in approximately 36% reduction in apparent oral clearance of methotrexate [see Drug Interactions (7)].

Other drugs: The coadministration of oxaprozin and antacids, acetaminophen, or conjugated estrogens resulted in no statistically significant changes in pharmacokinetic parameters in single- and/or multiple-dose studies. The interaction of oxaprozin with cardiac glycosides has not been studied.

13 NONCLINICAL TOXICOLOGY

13.1 Carcinogenesis, Mutagenesis, Impairment of Fertility

Carcinogenesis

In carcinogenicity studies in rats and mice, oxaprozin administration for 2 years was associated with the exacerbation of liver neoplasms (hepatic adenomas and carcinomas) in male CD mice, but not in female CD mice or male or female rats treated with up to 216 mg/kg via the diet (1.2-times the maximum daily human dose of 1800 mg based on body surface area). The significance of this species-specific finding to man is unknown.

Mutagenesis

Oxaprozin was not genotoxic in the Ames test, forward mutation in yeast and Chinese hamster ovary (CHO) cells, DNA repair testing in CHO cells, micronucleus testing in mouse bone marrow, chromosomal aberration testing in human lymphocytes, or cell transformation testing in mouse fibroblast.

Impairment of Fertility

Oxaprozin administration was not associated with impairment of fertility in male and female rats at oral doses up to 200 mg/kg/day (1.1-times the maximum recommended human daily dose [MRHD] of 1800 mg based on a body surface area comparison). However, testicular degeneration was observed in beagle dogs treated with 37.5 mg/kg/day (0.7-times the MRHD based on body surface area) of oxaprozin for 42 days or 6 months, a finding not confirmed in other species. The clinical relevance of this finding is not known.

14 CLINICAL STUDIES

14.1 Osteoarthritis

DAYPRO was evaluated for the management of the signs and symptoms of osteoarthritis in a total of 616 patients in active controlled clinical trials against aspirin (N=464), piroxicam (N=102), and other NSAIDs. DAYPRO was given both in variable (600 to 1200 mg/day) and in fixed (1200 mg/day) dosing schedules in either single or divided doses. In these trials, oxaprozin was found to be comparable to 2600 to 3200 mg/day doses of aspirin or 20 mg/day doses of piroxicam. Oxaprozin was effective both in once daily and in divided dosing schedules. In controlled clinical trials several days of oxaprozin therapy were needed for the drug to reach its full effects [see Dosage and Administration (2.5)].

14.2 Rheumatoid Arthritis

DAYPRO was evaluated for managing the signs and symptoms of rheumatoid arthritis in placebo and active controlled clinical trials in a total of 646 patients. DAYPRO was given in single or divided daily doses of 600 to 1800 mg/day and was found to be comparable to 2600 to 3900 mg/day of aspirin. At these doses there was a trend (over all trials) for oxaprozin to be more effective and cause fewer gastrointestinal side effects than aspirin.

DAYPRO was given as a once-a-day dose of 1200 mg in most of the clinical trials, but larger doses (up to 26 mg/kg or 1800 mg/day) were used in selected patients. In some patients, DAYPRO may be better tolerated in divided doses. Due to its long half-life, several days of DAYPRO therapy were needed for the drug to reach its full effect [see Dosage and Administration (2.5)].

16 HOW SUPPLIED/STORAGE AND HANDLING

DAYPRO (oxaprozin) 600 mg caplets are white, capsule-shaped, scored, film-coated, with DAYPRO debossed on one side and 1381 on the other side, supplied as:

NDC Number | Size
0025-1381-31 | bottle of 100
0025-1381-51 | bottle of 500
0025-1381-34 | carton of 100 unit dose

Storage

Keep bottles tightly closed. Store at room temperature 20°C to 25°C (68°F to 77°F); excursions permitted between 15°C to 30°C (59°F to 86°F) [see USP Controlled Room Temperature]. Dispense in a tight, light-resistant container with a child-resistant closure. Protect the unit dose from light.

17 PATIENT COUNSELING INFORMATION

Advise the patient to read the FDA-approved patient labeling (Medication Guide) that accompanies each prescription dispensed. Inform patients, families, or their caregivers of the following information before initiating therapy with DAYPRO and periodically during the course of ongoing therapy.

Cardiovascular Thrombotic Events

Advise patients to be alert for the symptoms of cardiovascular thrombotic events, including chest pain, shortness of breath, weakness, or slurring of speech, and to report any of these symptoms to their health care provider immediately [see Warnings and Precautions (5.1)].

Gastrointestinal Bleeding, Ulceration, and Perforation

Advise patients to report symptoms of ulcerations and bleeding, including epigastric pain, dyspepsia, melena, and hematemesis to their health care provider. In the setting of concomitant use of low-dose aspirin for cardiac prophylaxis, inform patients of the increased risk for and the signs and symptoms of GI bleeding [see Warnings and Precautions (5.2)].

Hepatotoxicity

Inform patients of the warning signs and symptoms of hepatotoxicity (e.g., nausea, fatigue, lethargy, pruritus, diarrhea, jaundice, right upper quadrant tenderness, and "flu-like" symptoms). If these occur, instruct patients to stop DAYPRO and seek immediate medical therapy [see Warnings and Precautions (5.3)].

Heart Failure and Edema

Advise patients to be alert for the symptoms of congestive heart failure including shortness of breath, unexplained weight gain, or edema and to contact their healthcare provider if such symptoms occur [see Warnings and Precautions (5.5)].

Anaphylactic Reactions

Inform patients of the signs of an anaphylactic reaction (e.g., difficulty breathing, swelling of the face or throat). Instruct patients to seek immediate emergency help if these occur [see Contraindications (4) and Warnings and Precautions (5.7)].

Serious Skin Reactions, including DRESS

Advise patients to stop taking DAYPRO immediately if they develop any type of rash or fever and to contact their healthcare provider as soon as possible [see Warnings and Precautions (5.9, 5.10)].

Female Fertility

Advise females of reproductive potential who desire pregnancy that NSAIDs, including DAYPRO, may be associated with a reversible delay in ovulation [see Use in Specific Populations (8.3)].

Fetal Toxicity

Inform pregnant women to avoid use of DAYPRO and other NSAIDs starting at 30 weeks gestation because of the risk of the premature closing of the fetal ductus arteriosus. If treatment with DAYPRO is needed for a pregnant woman between about 20 to 30 weeks gestation, advise her that she may need to be monitored for oligohydramnios, if treatment continues for longer than 48 hours [see Warnings and Precautions (5.11) and Use in Specific Populations (8.1)].

Avoid Concomitant Use of NSAIDs

Inform patients that the concomitant use of DAYPRO with other NSAIDs or salicylates (e.g., diflunisal, salsalate) is not recommended due to the increased risk of gastrointestinal toxicity, and little or no increase in efficacy [see Warnings and Precautions (5.2) and Drug Interactions (7)]. Alert patients that NSAIDs may be present in "over the counter" medications for treatment of colds, fever, or insomnia.

Use of NSAIDS and Low-Dose Aspirin

Inform patients not to use low-dose aspirin concomitantly with DAYPRO until they talk to their healthcare provider [see Drug Interactions (7)].

This product's labeling may have been updated. For the most recent prescribing information, please visit www.pfizer.com.

For medical information about DAYPRO, please visit www.pfizermedinfo.com or call 1-800-438-1985.

LAB-0189-15.0

Medication Guide for Nonsteroidal Anti-inflammatory Drugs (NSAIDs)

What is the most important information I should know about medicines called Nonsteroidal Anti-inflammatory Drugs (NSAIDs)?

NSAIDs can cause serious side effects, including:

- Increased risk of a heart attack or stroke that can lead to death. This risk may happen early in treatment and may increase:
  - with increasing doses of NSAIDs
  - with longer use of NSAIDs

Do not take NSAIDs right before or after a heart surgery called a "coronary artery bypass graft (CABG)".

Avoid taking NSAIDs after a recent heart attack, unless your healthcare provider tells you to. You may have an increased risk of another heart attack if you take NSAIDs after a recent heart attack.

- Increased risk of bleeding, ulcers, and tears (perforation) of the esophagus (tube leading from the mouth to the stomach), stomach and intestines:
  - anytime during use
  - without warning symptoms
  - that may cause death

- The risk of getting an ulcer or bleeding increases with:
  - past history of stomach ulcers, or stomach or intestinal bleeding with use of NSAIDs
  - taking medicines called "corticosteroids", "antiplatelet drugs", "anticoagulants", "SSRIs", "SNRIs"

- increasing doses of NSAIDs
- longer use of NSAIDs
- smoking
- drinking alcohol

- older age
- poor health
- advanced liver disease
- bleeding problems

- NSAIDs should only be used:
  - exactly as prescribed
  - at the lowest dose possible for your treatment
  - for the shortest time needed

What are NSAIDs?

NSAIDs are used to treat pain and redness, swelling, and heat (inflammation) from medical conditions such as different types of arthritis, menstrual cramps, and other types of short-term pain.

Who should not take NSAIDs?

Do not take NSAIDs:

- if you have had an asthma attack, hives, or other allergic reaction with aspirin or any other NSAIDs.
- right before or after heart bypass surgery.

Before taking NSAIDS, tell your healthcare provider about all of your medical conditions, including if you:

- have liver or kidney problems
- have high blood pressure
- have asthma
- are pregnant or plan to become pregnant. Taking NSAIDs at about 20 weeks of pregnancy or later may harm your unborn baby. If you need to take NSAIDs for more than 2 days when you are between 20 and 30 weeks of pregnancy, your healthcare provider may need to monitor the amount of fluid in your womb around your baby. You should not take NSAIDs after about 30 weeks of pregnancy.
- are breastfeeding or plan to breast feed.

Tell your healthcare provider about all of the medicines you take, including prescription or over-the-counter medicines, vitamins or herbal supplements. NSAIDs and some other medicines can interact with each other and cause serious side effects. Do not start taking any new medicine without talking to your healthcare provider first.

What are the possible side effects of NSAIDs?

NSAIDs can cause serious side effects, including:

See "What is the most important information I should know about medicines called Nonsteroidal Anti-inflammatory Drugs (NSAIDs)?"

- new or worse high blood pressure
- heart failure
- stroke
- liver problems including liver failure
- kidney problems including kidney failure
- low red blood cells (anemia)
- life-threatening skin reactions
- life-threatening allergic reactions
- asthma attacks in people who have asthma
- bleeding and ulcers in the stomach and intestine
- Other side effects of NSAIDs include: stomach pain, constipation, diarrhea, gas, heartburn, nausea, vomiting, and dizziness.

Get emergency help right away if you get any of the following symptoms:

- shortness of breath or trouble breathing
- chest pain
- weakness in one part or side of your body

- slurred speech
- swelling of the face or throat

Stop taking your NSAID and call your healthcare provider right away if you get any of the following symptoms:

- nausea
- more tired or weaker than usual
- diarrhea
- itching
- your skin or eyes look yellow
- indigestion or stomach pain
- flu-like symptoms

- vomit blood
- there is blood in your bowel movement or it is black and sticky like tar
- unusual weight gain
- skin rash or blisters with fever
- swelling of the arms, legs, hands and feet

If you take too much of your NSAID, call your healthcare provider or get medical help right away.

These are not all the possible side effects of NSAIDs. For more information, ask your healthcare provider or pharmacist about NSAIDs.

Call your doctor for medical advice about side effects. You may report side effects to FDA at 1-800-FDA-1088.

Other information about NSAIDs

- Aspirin is an NSAID but it does not increase the chance of a heart attack. Aspirin can cause bleeding in the brain, stomach, and intestines. Aspirin can also cause ulcers in the stomach and intestines.
- Some NSAIDs are sold in lower doses without a prescription (over-the-counter). Talk to your healthcare provider before using over-the-counter NSAIDs for more than 10 days.

General information about the safe and effective use of NSAIDs

Medicines are sometimes prescribed for purposes other than those listed in a Medication Guide. Do not use NSAIDs for a condition for which it was not prescribed. Do not give NSAIDs to other people, even if they have the same symptoms that you have. It may harm them.

If you would like more information about NSAIDs, talk with your healthcare provider. You can ask your pharmacist or healthcare provider for information about NSAIDs that is written for health professionals.

This product's labeling may have been updated. For the most recent prescribing information, please visit www.pfizer.com.

LAB-0791-6.0

This Medication Guide has been approved by the U.S. Food and Drug Administration. Revised: November 2024

PRINCIPAL DISPLAY PANEL - 600 mg Caplet Bottle Label

ALWAYS DISPENSE WITH MEDICATION GUIDE

NDC 0025-1381-31

Pfizer

Daypro ®
(oxaprozin) caplets

600 mg

100 Caplets
Rx only